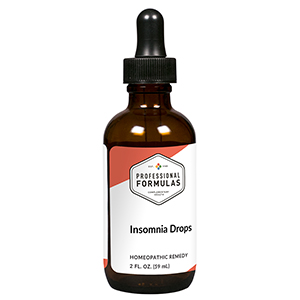 DRUG LABEL: Insomnia Drops
NDC: 63083-2035 | Form: LIQUID
Manufacturer: Professional Complementary Health Formulas
Category: homeopathic | Type: HUMAN OTC DRUG LABEL
Date: 20190815

ACTIVE INGREDIENTS: ARTEMISIA ANNUA FLOWERING TOP 1 [hp_X]/59 mL; VALERIAN 1 [hp_X]/59 mL; AVENA SATIVA FLOWERING TOP 2 [hp_X]/59 mL; ZINC 3 [hp_X]/59 mL; PASSIFLORA INCARNATA FLOWERING TOP 6 [hp_X]/59 mL; ARABICA COFFEE BEAN 6 [hp_X]/59 mL; PAULLINIA CUPANA SEED 24 [hp_X]/59 mL
INACTIVE INGREDIENTS: ALCOHOL; WATER

C35

ACTIVE INGREDIENTS

Chamomilla 1X
Valeriana officinalis 1X
Avena sativa 2X
Zincum metallicum 3X
Passiflora incarnata 6X
Coffea cruda 6X, 12X, 30X
Paullinia sorbilis 24X

QUESTIONS

Professional Formulas

PO Box 2034 Lake Oswego, OR 97035

INDICATIONS

For the temporary relief of difficulty falling or staying asleep.*

PURPOSE

*Claims based on traditional homeopathic practice, not accepted medical evidence. Not FDA evaluated.

WARNINGS

In case of overdose, get medical help or contact a poison control center right away.

Keep out of the reach of children.

PREGNANCY OR BREAST FEEDING

If pregnant or breastfeeding, ask a healthcare professional before use.

DIRECTIONS

Place drops under tongue 30 minutes before/after meals. Adults and children 12 years and over: Take 10 drops up to 3 times per day for up to 6 weeks. For immediate onset of symptoms, take 10 to 15 drops every 15 minutes up to 3 hours. For less severe symptoms, take 10-15 drops hourly up to 8 hours. Consult a physician for use in children under 12 years of age.

OTHER INFORMATION

Tamper resistant. If seal is broken, do not use. After opening, close container tightly and store at room temperature away from heat.

INACTIVE INGREDIENTS

20% ethanol, purified water.

LABEL

Est 1985

Professional Formulas

Complementary Health

Insomnia Drops

Homeopathic Remedy

2 FL. OZ. (59 mL)